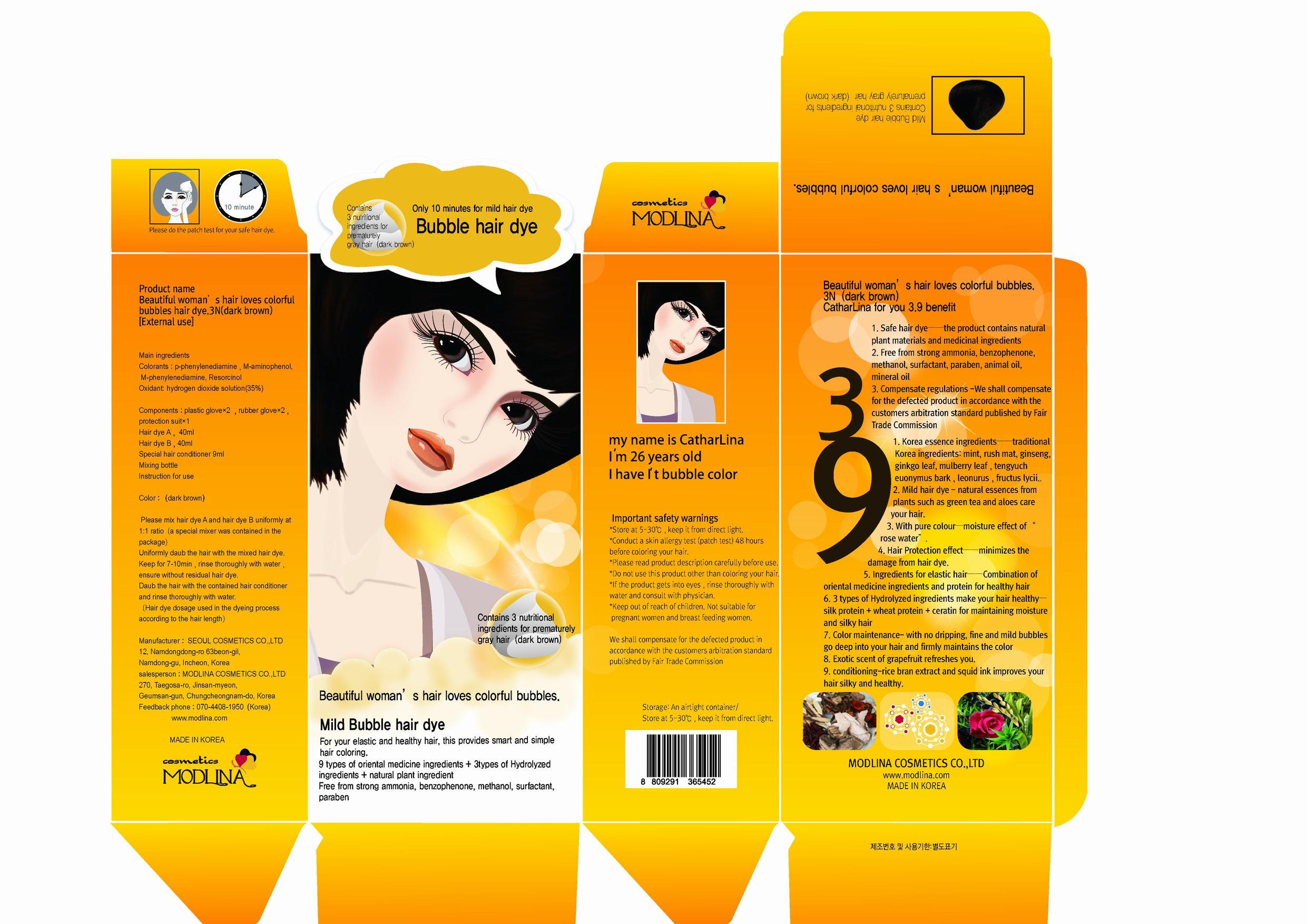 DRUG LABEL: BEAUTIFUL WOMANS HAIR LOVES COLORFUL BUBBLES HAIR DYE 3N DARK BROWN
NDC: 58895-3001 | Form: LIQUID
Manufacturer: Modlina Cosmetics Co., Ltd
Category: otc | Type: HUMAN OTC DRUG LABEL
Date: 20130816

ACTIVE INGREDIENTS: P-PHENYLENEDIAMINE 0.01 mg/1 mL
INACTIVE INGREDIENTS: M-AMINOPHENOL; RESORCINOL; M-PHENYLENEDIAMINE

Drug Facts

ACTIVE INGREDIENT

P-PHENYLENEDIAMINE

INACTIVE INGREDIENT

m-aminophenol, m-phenylenediamine, resorcinol, hydrogen dioxide

PURPOSE

hair coloring

keep out of reach of the children

INDICATIONS AND USAGE

Please mix hair dye A and hair dye B uniformly at 1:1 ratio（a special mixer was contained in the package）
Uniformly daub the hair with the mixed hair dye.
Keep for 7-10min，rinse thoroughly with water，ensure without residual hair dye.
Daub the hair with the contained hair conditioner and rinse thoroughly with water.
（Hair dye dosage used in the dyeing process according to the hair length

WARNINGS

if you notice any skin trouble or other unexpected reaction such as rash, irritation discontinue use immediately and ask a doctor
do not expose this product directly to the sun and store in a cool dry place

DOSAGE AND ADMINISTRATION

for external use only